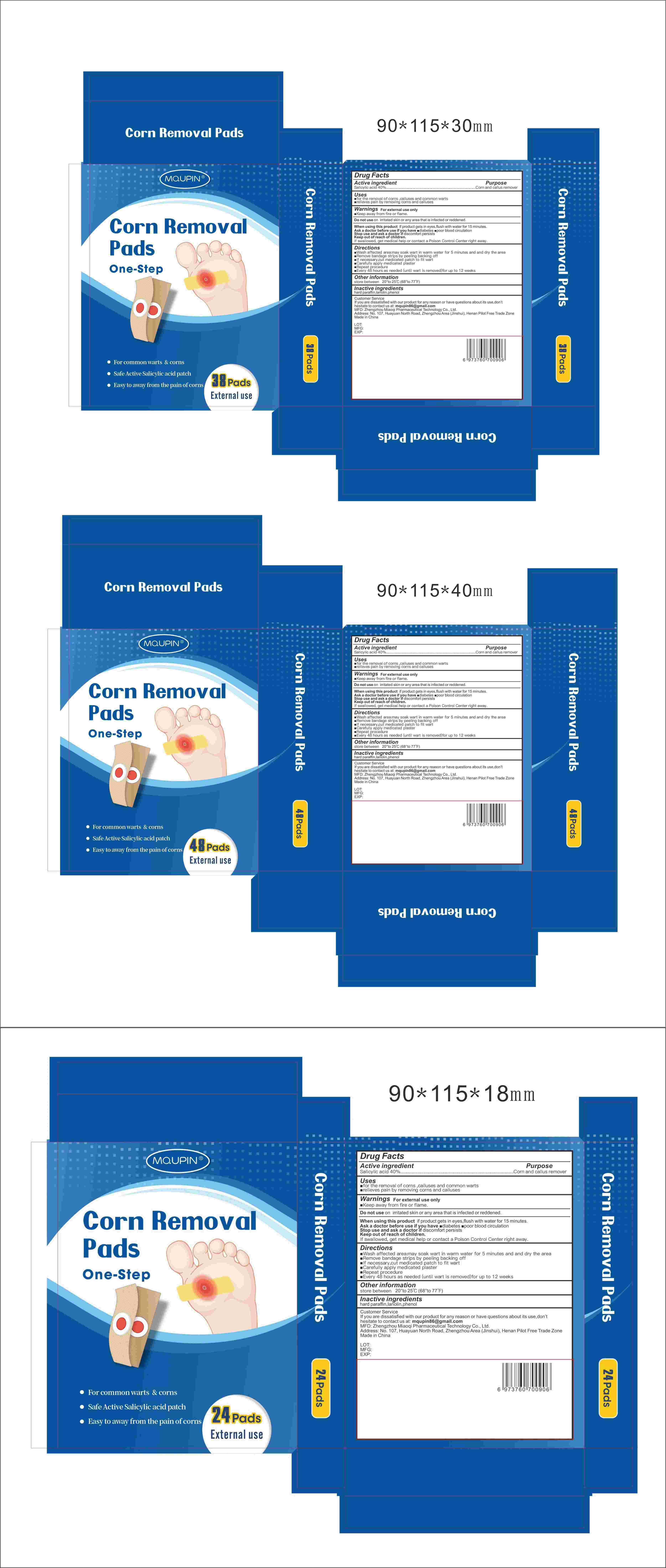 DRUG LABEL: MQUPIN Corn Removal Pads
NDC: 83781-001 | Form: PATCH
Manufacturer: Zhengzhou Miaoqi Pharmaceutical Technology Co., Ltd
Category: otc | Type: HUMAN OTC DRUG LABEL
Date: 20250324

ACTIVE INGREDIENTS: SALICYLIC ACID 40 g/100 1
INACTIVE INGREDIENTS: PARAFFIN; LANOLIN; PHENOL

83781-001 Update V2

Active Ingredient

Salicylic Acid 40%

Purpose

Corn and callus remover

Use

■for the removal of corns,calluses and common warts
relieves pain by removing corns and calluses

Warnings

■ For external use only

■Keep away from fire and flame

Do not use

on irritated skin or any area that is infected or reddened

When Using

if product gets in eyes,flush with water for 15 minutes.

Stop Use

discomfort persists

Ask Doctor

Ask a doctor before use if you have

■diabetes

■ poor blood circulation

Keep out of reach of children.If swallowed,get medical help or contact a Poison Control Center right away.

Directions

■ Wash affected area:may soak wart in warm water for 5 minutes and and dry the area Remove bandage strips by peeling backing off

■lf necessary,cut medicated patch to fit wart

■Carefully apply medicated plaster

■Repeat procedure

■Every 48 hours as needed (until wart is removed)for up to 12 weeks

Other information

■ store between 20°to 25°C (68° to 77°F)

Inactive ingredients

hard paraffin,lanolin,phenol

Questions

mqupin86@gmail.com